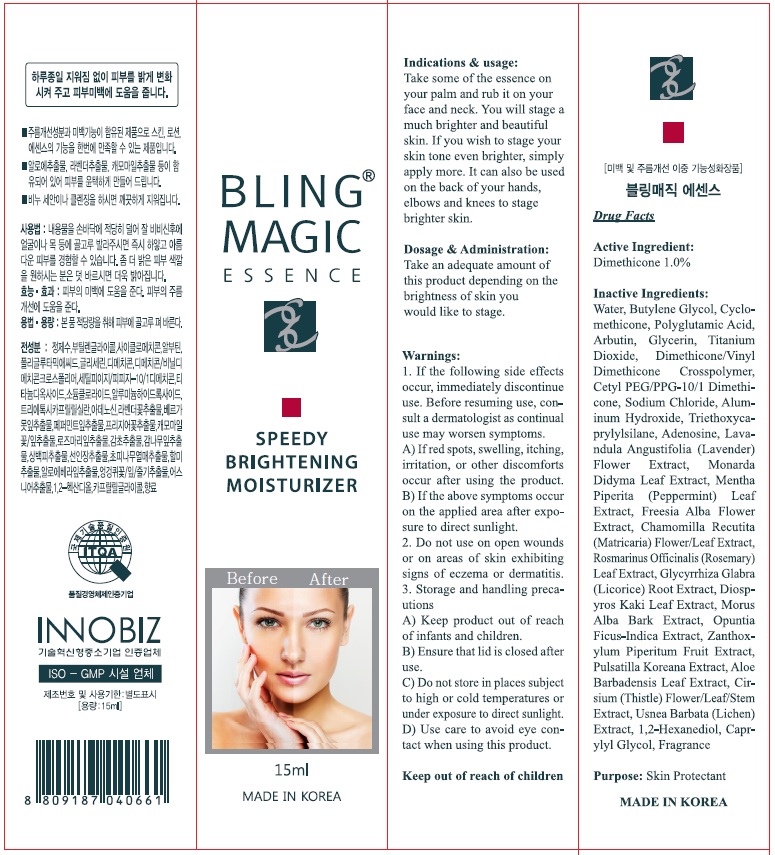 DRUG LABEL: Bling Magic Speedy Brightening Moisturizer
NDC: 70653-010 | Form: CREAM
Manufacturer: GRU INTERNATIONAL
Category: otc | Type: HUMAN OTC DRUG LABEL
Date: 20160509

ACTIVE INGREDIENTS: Dimethicone 0.15 g/15 mL
INACTIVE INGREDIENTS: Water; Butylene Glycol

ACTIVE INGREDIENT

Active Ingredient: Dimethicone 1.0%

INACTIVE INGREDIENT

Inactive Ingredients: Water, Butylene Glycol, Cyclomethicone, Polyglutamic Acid, Arbutin, Glycerin, Titanium Dioxide, Dimethicone/Vinyl Dimethicone Crosspolymer, Cetyl PEG/PPG-10/1 Dimethicone, Sodium Chloride, Aluminum Hydroxide, Triethoxycaprylylsilane, Adenosine, Lavandula Angustifolia (Lavender) Flower Extract, Monarda Didyma Leaf Extract, Mentha Piperita (Peppermint) Leaf Extract, Freesia Alba Flower Extract, Chamomilla Recutita (Matricaria) Flower/Leaf Extract, Rosmarinus Officinalis (Rosemary) Leaf Extract, Glycyrrhiza Glabra (Licorice) Root Extract, Diospyros Kaki Leaf Extract, Morus Alba Bark Extract, Opuntia Ficus-Indica Extract, Zanthoxylum Piperitum Fruit Extract, Pulsatilla Koreana Extract, Aloe Barbadensis Leaf Extract, Cirsium (Thistle) Flower/Leaf/Stem Extract, Usnea Barbata (Lichen) Extract, 1,2-Hexanediol, Caprylyl Glycol, Fragrance

PURPOSE

Purpose: Skin Protectant

WARNINGS

Warnings: 1. If the following side effects occur, immediately discontinue use. Before resuming use, consult a dermatologist as continual use may worsen symptoms. A) If red spots, swelling, itching, irritation, or other discomforts occur after using the product. B) If the above symptoms occur on the applied area after exposure to direct sunlight. 2. Do not use on open wounds or on areas of skin exhibiting signs of eczema or dermatitis. 3. Storage and handling precautions A) Keep product out of reach of infants and children. B) Ensure that lid is closed after use. C) Do not store in places subject to high or cold temperatures or under exposure to direct sunlight. D) Use care to avoid eye contact when using this product.

KEEP OUT OF REACH OF CHILDREN

Keep product out of reach of infants and children.

INDICATIONS & USAGE

Indications & usage: Take some of the essence on your palm and rub it on your face and neck. You will stage a much brighter and beautiful skin. If you wish to stage your skin tone even brighter, simply apply more. It can also be used on the back of your hands, elbows and knees to stage brighter skin.

DOSAGE & ADMINISTRATION

Dosage & Administration: Take an adequate amount of this product depending on the brightness of skin you would like to stage.